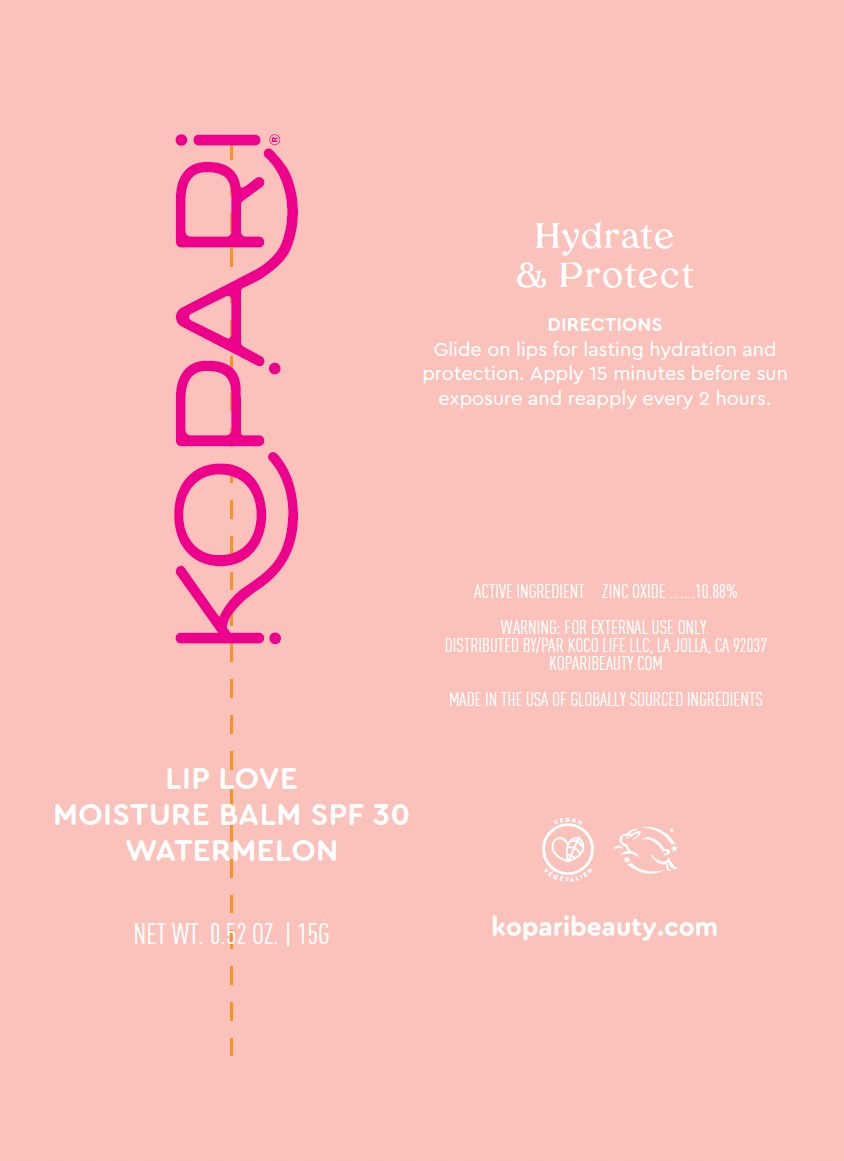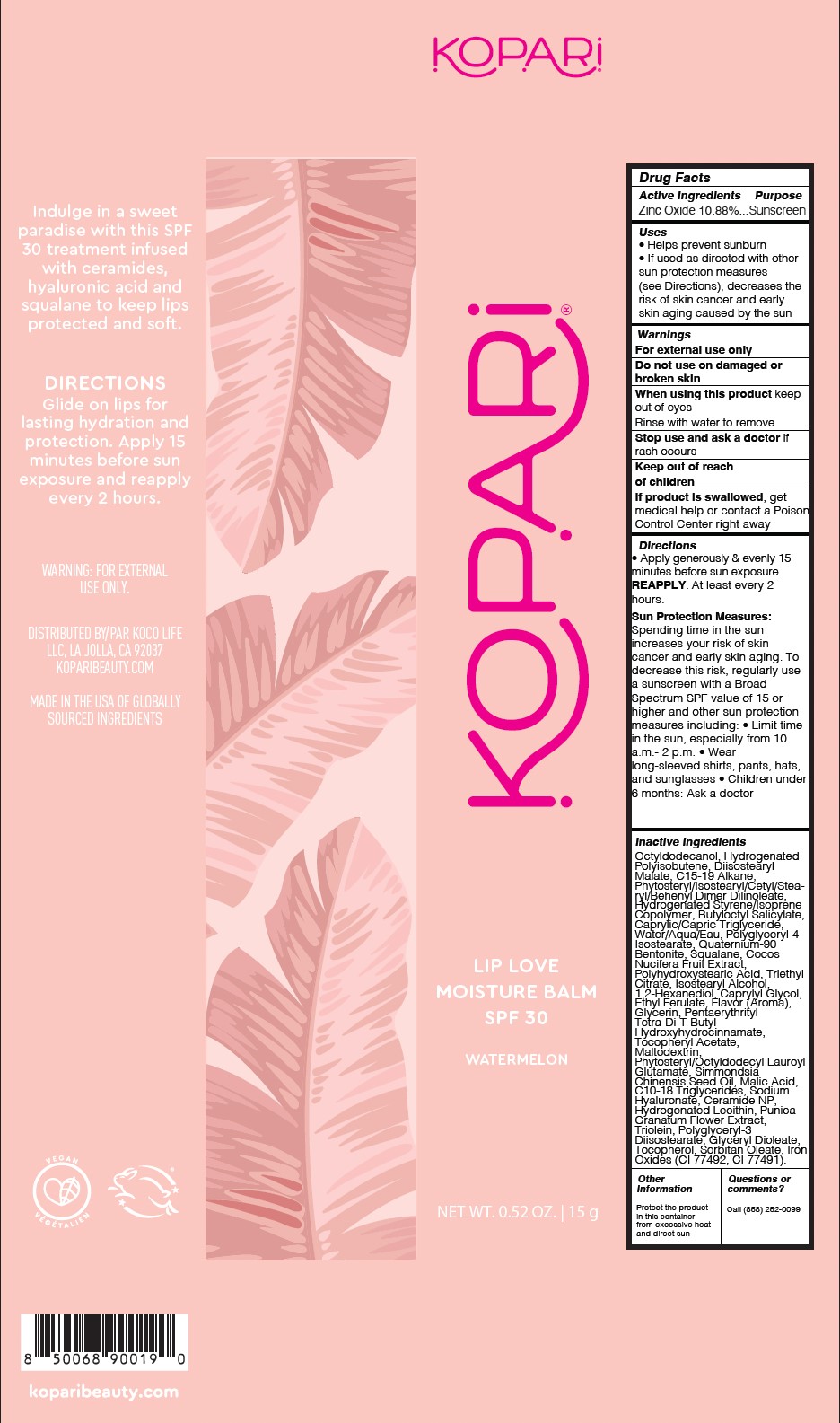 DRUG LABEL: Lip Love Moisture Balm SPF30 - Watermelon
NDC: 84130-016 | Form: GEL
Manufacturer: Koco Life LLC
Category: otc | Type: HUMAN OTC DRUG LABEL
Date: 20250507

ACTIVE INGREDIENTS: ZINC OXIDE 10.88 g/100 g
INACTIVE INGREDIENTS: GLYCERIN; PENTAERYTHRITYL TETRA-DI-T-BUTYL HYDROXYHYDROCINNAMATE; POLYGLYCERYL-4 ISOSTEARATE; QUATERNIUM-90 BENTONITE; PHYTOSTERYL/ISOSTEARYL/CETYL/STEARYL/BEHENYL DIMER DILINOLEATE; BUTYLOCTYL SALICYLATE; ISOSTEARYL ALCOHOL; PUNICA GRANATUM FLOWER; GLYCERYL DIOLEATE; CI 77491; SORBITAN OLEATE; ALPHA-TOCOPHEROL ACETATE; MALTODEXTRIN; TRIOLEIN; SQUALANE; POLYHYDROXYSTEARIC ACID (2300 MW); 1,2-HEXANEDIOL; SIMMONDSIA CHINENSIS (JOJOBA) SEED OIL; MALIC ACID; CI 77492; PHYTOSTERYL/OCTYLDODECYL LAUROYL GLUTAMATE; CERAMIDE NP; DIISOSTEARYL MALATE; TRIETHYL CITRATE; OCTYLDODECANOL; HYDROGENATED POLYISOBUTENE 8; C15-19 ALKANE; CAPRYLIC/CAPRIC TRIGLYCERIDE; WATER; COCOS NUCIFERA (COCONUT) FRUIT; CAPRYLYL GLYCOL; ETHYL FERULATE; C10-18 TRIGLYCERIDES; SODIUM HYALURONATE; HYDROGENATED SOYBEAN LECITHIN; POLYGLYCERYL-3 DIISOSTEARATE; TOCOPHEROL

Lip Love Moisture Balm SPF30 - Watermelon

Active ingredient

Zinc Oxide 10.88%

Purpose

Zinc Oxide 10.88%...Sunscreen

Uses

• Helps prevent sunburn

• If used as directed with othersun protection measures(see Directions), decreases therisk of skin cancer and earlyskin aging caused by the sun

Warnings

For external use only

Do not use on damaged or broken skin

When using this product keep out of eyes

Rinse with water to remove

Stop use and ask a doctor if rash occurs

Keep out of reach of children
If product is swallowed , get medical help or contact a Poison Control Center right away

Directions

• Apply generously & evenly 15 minutes before sun exposure. REAPPLY: At least every 2 hours.

Sun Protection Measures:Spending time in the sun increases your risk of skin cancer and early skin aging. To decrease this risk, regularly use a sunscreen with a Broad Spectrum SPF value of 15 or higher and other sun protection measures including: • Limit time in the sun, especially from 10 a.m.- 2 p.m. • Wearlong-sleeved shirts, pants, hats, and sunglasses • Children under 6 months: Ask a doctor

Inactive ingredients

Octyldodecanol, Hydrogenated Polyisobutene, Diisostearyl Malate, C15-19 Alkane, Phytosteryl/Isostearyl/Cetyl/Stearyl/Behenyl Dimer Dilinoleate, Hydrogenated Styrene/Isoprene Copolymer, Butyloctyl Salicylate, Caprylic/Capric Triglyceride, Water/Aqua/Eau, Polyglyceryl-4 Isostearate, Quaternium-90 Bentonite, Squalane, Cocos Nucifera Fruit Extract, Polyhydroxystearic Acid, Triethyl Citrate, Isostearyl Alcohol, 1,2-Hexanediol, Caprylyl Glycol, Ethyl Ferulate, Flavor (Aroma), Glycerin, PentaerythritylTetra-Di-T-Butyl Hydroxyhydrocinnamate, Tocopheryl Acetate, Maltodextrin, Phytosteryl/Octyldodecyl Lauroyl Glutamate, Simmondsia Chinensis Seed Oil, Malic Acid, C10-18 Triglycerides, Sodium Hyaluronate, Ceramide NP, Hydrogenated Lecithin, Punica Granatum Flower Extract, Triolein, Polyglyceryl-3 Diisostearate, Glyceryl Dioleate, Tocopherol, Sorbitan Oleate, Iron Oxides (CI 77492, CI 77491)

Other information

Protect the product in this container from excessive heat and direct sun

Questions or comments?

Call (858) 252-0099